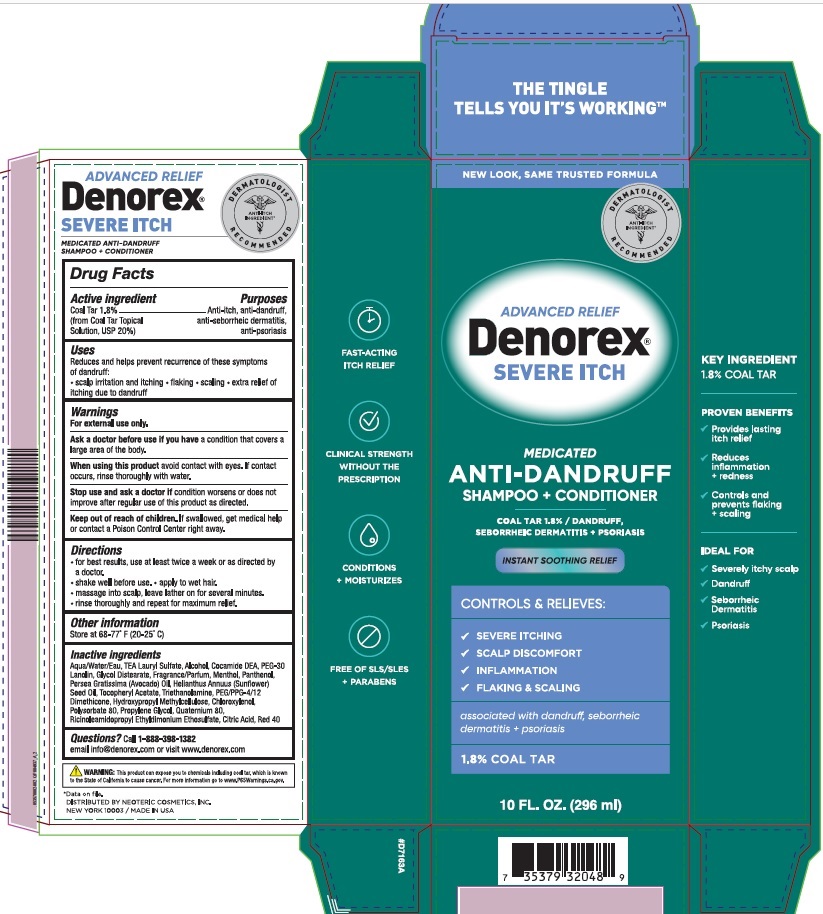 DRUG LABEL: Denorex Severe Itch
NDC: 62673-175 | Form: SHAMPOO
Manufacturer: Neoteric Cosmetics, Inc.
Category: otc | Type: HUMAN OTC DRUG LABEL
Date: 20240903

ACTIVE INGREDIENTS: COAL TAR 0.018 g/1 mL
INACTIVE INGREDIENTS: TRIETHANOLAMINE SULFATE; PEG/PPG-4/12 DIMETHICONE; COCO DIETHANOLAMIDE; ALCOHOL; AVOCADO OIL; CHLOROXYLENOL; CITRIC ACID MONOHYDRATE; FD&C RED NO. 40; GLYCOL DISTEARATE; HYPROMELLOSES; PANTHENOL; RICINOLEAMIDOPROPYL ETHYLDIMONIUM ETHOSULFATE; .ALPHA.-TOCOPHEROL ACETATE; WATER; SUNFLOWER OIL; PEG-30 LANOLIN; TROLAMINE; POLYSORBATE 80; PROPYLENE GLYCOL; QUATERNIUM-80; MENTHOL

Denorex Severe Itch

Drug Facts

Active Ingredients:

Coal Tar 1.8%
(from Coal Tar Topical Solution, USP 20%)

Purpose:

Anti-itch, anti-dandruff, anti-seborrheic dermatitis, anti-psoriasis

Uses:

Reduces and helps prevent recurrence of these symptoms of dandruff:

- scalp irritation and itching • flaking • scaling • extra relief of itching due to dandruff

Warnings:

For external use only

Ask a doctor before use if you have

a condition covers a large area of the body.

When using this product

avoid contact with eyes. If contact occurs, rinse thoroughly with water

Stop use and ask a doctor

if condition worsens or does not improve after regular use of this product as directed.

Keep out of reach of children.

If swallowed, get medical help or contact a Poison Control Center right away.

Directions:

- for best results, use at least twice a week or as directed by a doctor
- shake well before use
- apply to wet hair
- massage into scalp, leave lather on for several minutes
- rinse thoroughly and repeat for maximum relief

Other information

Store at 68-77°F (20-25°C)

Inactive ingredients

Aqua/Water/Eau, TEA Lauryl Sulfate, Alcohol, Cocamide DEA, PEG-30 Lanolin, Glycol Distearate, Fragrance/Parfum, Menthol, Panthenol, Persea Gratissima (Avocado) Oil, Helianthus Annuus (Sunflower) Seed Oil, Tocopheryl Acetate, Triethanolamine, PEG/PPG-4/12 Dimethicone, Hydroxypropyl Methylcellulose, Chloroxylenol, Polysorbate 80, Propylene Glycol, Quaternium 80, Ricinoleamidopropyl Ethyldimonium Ethosulfate, Citric Acid, Red 40

Questions?

Call 1-888-398-1382

email info@denorex.com or visit www.denorex.com

WARNING:

This product can expose you to chemicals including coal tar, which is known to the State of California to cause cancer. For more information go to www.P65Warnings.ca.gov.

PACKAGE LABEL

ADVANCED RELIEF
Denorex®
SEVERE ITCH

MEDICATED

ANTI-DANDRUFF

SHAMPOO + CONDITIONER

1.8 % Coal Tar / DANDRUFF,

SEBORRHEIC DERMATITIS + PSORIASIS
INSTANT SOOTHING RELIEF
CONTROLS & RELIEVES:

SEVERE ITCHING

SCALP DISCOMFORT

INFLAMMATION

FLAKING & SCALING

associated with dandruff, seborrheic dermatitis + psoriasis

1.8% COAL TAR
10 FL OZ (296 mL)